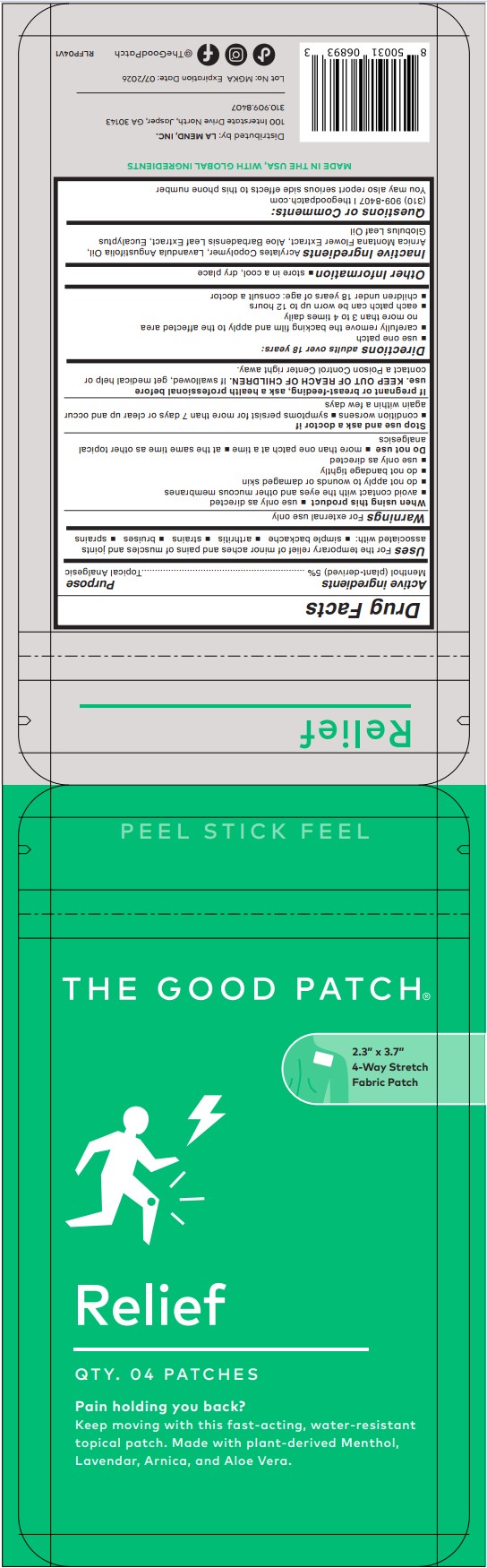 DRUG LABEL: Relief
NDC: 72587-003 | Form: PATCH
Manufacturer: La Mend, Inc.
Category: otc | Type: HUMAN OTC DRUG LABEL
Date: 20240801

ACTIVE INGREDIENTS: MENTHOL 5 g/100 g
INACTIVE INGREDIENTS: LAVENDER OIL; ARNICA MONTANA FLOWER; EUCALYPTUS OIL; ALOE VERA LEAF

Relief

Active ingredients

Menthol (plant derived) 5%

Purpose

Menthol (plant derived) 5%....................Topical Analgesic

Uses

For the temporary relief of minor aches and pains of muscles and joints associated with:

- simple backache
- arthritis
- strains
- bruises
- sprains

Warnings

For external use only

When using this product

- use only as directed
- avoid contact with the eyes and other mucous membranes
- do not apply to wounds or damaged skin
- do not bandage tightly
- use only as directed

Do not use

- more than one patch at a time
- at the same time as other topical analgesics

Stop use and ask a doctor if

- condition worsens
- symptoms persist for more than 7 days or clear up and occur again within a few days

PREGNANCY OR BREAST FEEDING

If pregnant or breast-feeding, ask a health professional before use.

KEEP OUT OF REACH OF CHILDREN. If swallowed, get medical help or contact a Posion Control Center right away.

Directions

adults over 18 years:

- use one patch
- carefully remove the backing film and apply to the affected area no more than 3 to 4 times daily
- each patch can be worn up to 12 hours
- children under 18 years of age: consult a doctor

Other information

- store in a cool, dry place

Inactive ingredients

Acrylates Copolymer, Lavandula Angustifolia Oil, Arnica Montana Flower Extract, Aloe Barbadensis Leaf Extract, Eucalyptus Globulus Leaf Oil

Questions or Comments

(310) 909-8407 | thegoodpatch.com

You may also report serious side effects to this phone number

PACKAGE LABEL

The Good Patch

Relief

QTY. 04 PATCHES

Pain holding you back? Keep moving with this fast-acting, water-resistant topical patch. Made with plant-derived Menthol, Lavender, Arnica, and Aloe Vera.